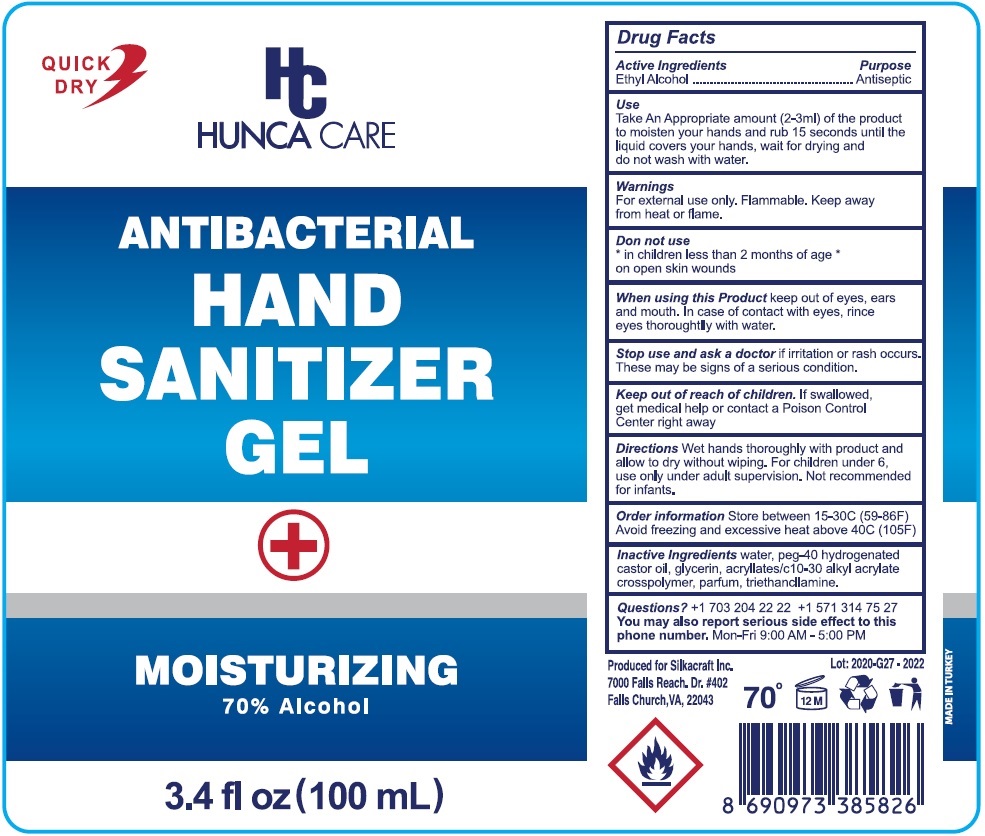 DRUG LABEL: HUNCA CARE STOP BAC
NDC: 78379-002 | Form: GEL
Manufacturer: HUNCA KOZMETIK SANAYII ANONIM SIRKETI
Category: otc | Type: HUMAN OTC DRUG LABEL
Date: 20200609

ACTIVE INGREDIENTS: ALCOHOL 70 L/100 L
INACTIVE INGREDIENTS: WATER; POLYOXYL 40 HYDROGENATED CASTOR OIL; GLYCERIN; CARBOMER INTERPOLYMER TYPE A (ALLYL SUCROSE CROSSLINKED); TROLAMINE

HUNCA CARE ANTIBACTERIAL HAND SANITIZER GEL

Active Ingredients

Ethyl Alcohol

Purpose

Antiseptic

Use

Take An Appropriate amount (2-3ml) of the product to moisten your hands and rub 15 seconds until the liquid covers your hands,

wait for drying and do not wash with water.

Warnings

For external use only. Flammable. Keep away from heat or flame.

Do not use

* in children less than 2 months of age

* on open skin wounds

When using this product keep out of eyes, ears, and mouth. In case of contact with eyes, rinse eyes thoroughly with water.

Stop use and ask a doctor if irritation or rash occurs. These may be signs of a serious condition.

Keep out of reach of children. If swallowed, get medical help or contact a Poison Control Center right away.

DOSAGE AND ADMINISTRATION

Directions Wet hands thoroughly with product and allow to dry without wiping. For children under 6, use only under adult supervision.

Not recommended for infants.

STORAGE AND HANDLING

Order information Store between 15-30°C (59-86°F)

Avoid freezing and excessive heat above 40°C (105°F)

INACTIVE INGREDIENT

Inactive Ingredients water, peg-40 hydrogenated castor oil, glycerin, acrylates/c 10-30 alkyl acrylate crosspolymer, parfum, triethanolamine.

QUESTIONS

Questions?+1 703 204 22 22 +1 571 314 75 27

You may also report serious side effect to this phone number. Mon-Fri 9:00 AM - 5:00 PM

QUICK DRY

MOISTURIZING

70% Alcohol

Produced for Silkacraft Inc.

7000 Falls Reach. Dr. #402

Falls Church, VA, 22043

MADE IN TURKEY